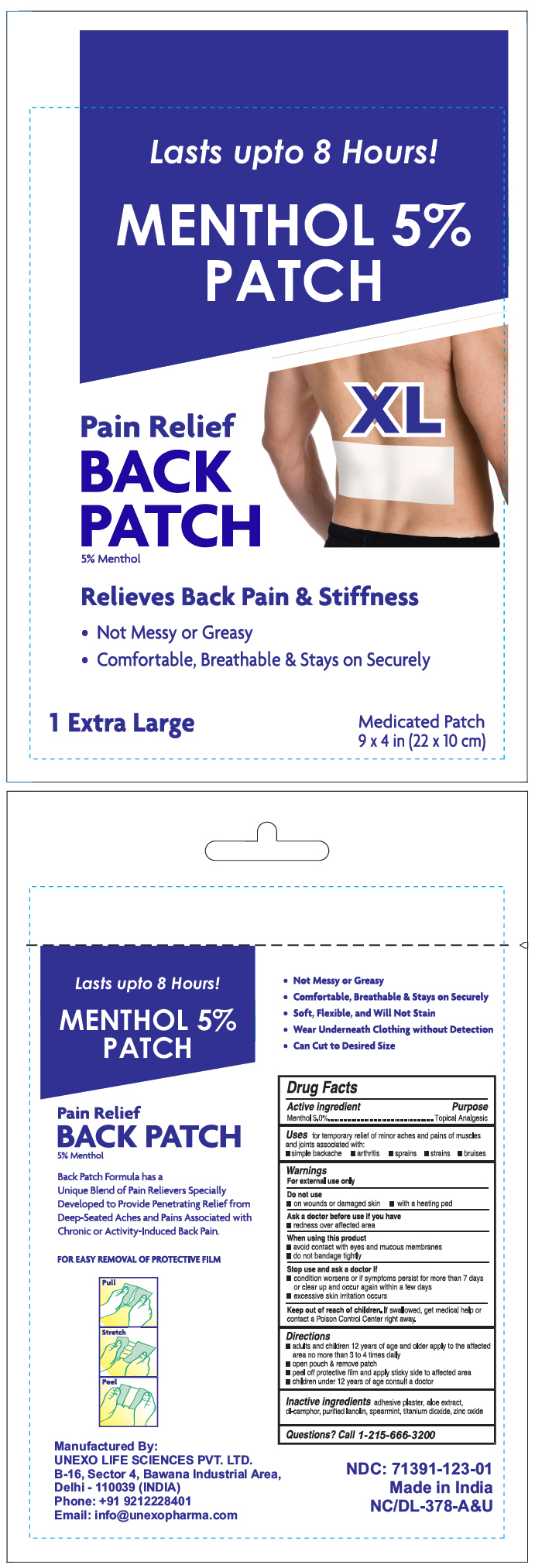 DRUG LABEL: Menthol 5%
NDC: 71391-123 | Form: PATCH
Manufacturer: Unexo Life Sciences, Private Limited
Category: otc | Type: HUMAN OTC DRUG LABEL
Date: 20250110

ACTIVE INGREDIENTS: MENTHOL, UNSPECIFIED FORM 440 mg/1 1
INACTIVE INGREDIENTS: ALOE; Camphor (synthetic); Lanolin; Spearmint; Titanium Dioxide; Zinc Oxide

Menthol Patch 5% Patch

Drug Facts

Active Ingredient

PURPOSE

Menthol 5% - Topical Analgesic

Uses

For temporary relief of minor aches and pains of muscles and joints associated with:

- Simple backache
- Arthritis
- Sprains
- Strains
- Bruises

Warnings

For external use only

Do not use

- On wounds or damaged skin
- With a heating pad

Ask a doctor before use if you have

- Redness over affected area

When using this product

- Avoid contact with eyes and mucous membranes
- Do not bandage tightly

Stop use and ask a doctor if

- Condition worsens or if symptoms persist for more than 7 days or clear up and occur again within a few days
- Excessive skin irritation occurs

Keep out of reach of children. If swallowed, get medical help or contact a Poison Control Center right away.

Directions

- Adults and children 12 years of age and older apply to the affected area no more than 3 to 4 times daily
- Open pouch & remove patch
- Peel off protective film and apply sticky side to affected area
- Children under 12 years of age consult a doctor

Inactive Ingredients

Adhesive plaster, aloe extract, dl-camphor, purified lanolin, spearmint, titanium dioxide, zinc oxide

Questions

Call 1-215-666-3200

Manufactured By:
UNEXO LIFE SCIENCES PVT. LTD.
B-16. Sector 4, Bawana Industrial Area,
Delhi – 110039 (INDIA)

PRINCIPAL DISPLAY PANEL - 1 Patch Pouch

Lasts upto 8 Hours!

MENTHOL 5%
PATCH

XL

Pain Relief
BACK
PATCH
5% Menthol

Relieves Back Pain & Stiffness

• Not Messy or Greasy
• Comfortable, Breathable & Stays on Securely

1 Extra Large
Medicated Patch
9 x 4 in (22 x 10 cm)